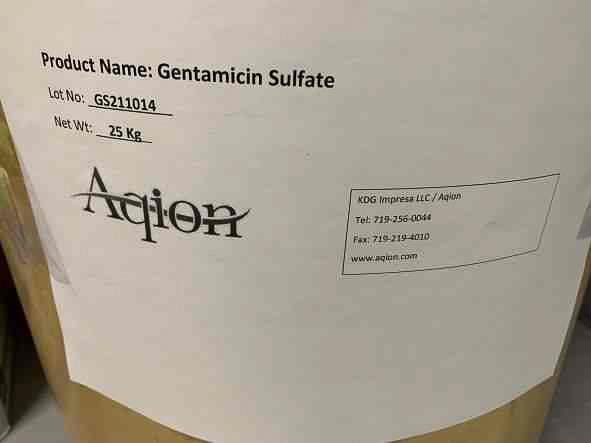 DRUG LABEL: Gentamicin Sulfate
NDC: 43457-533 | Form: POWDER
Manufacturer: KDG Impresa LLC, Aqion
Category: other | Type: BULK INGREDIENT - ANIMAL DRUG
Date: 20220128

ACTIVE INGREDIENTS: GENTAMICIN SULFATE 1 kg/1 kg

Gentamicin Sulfate